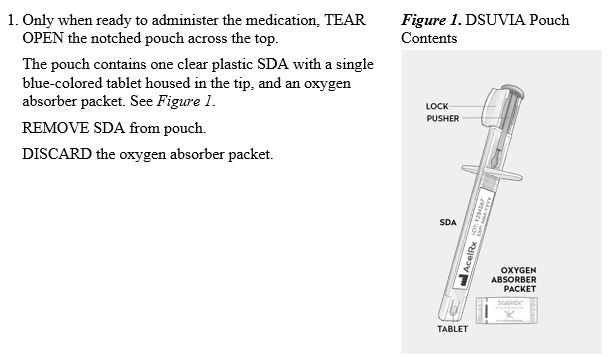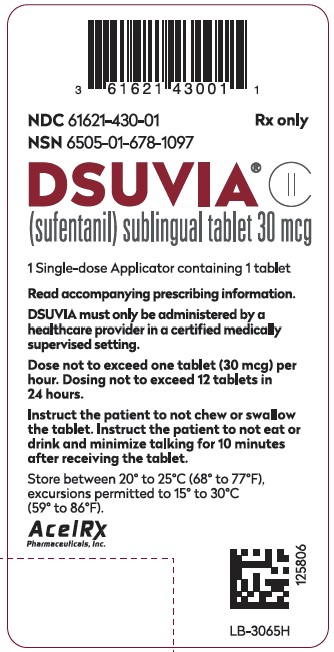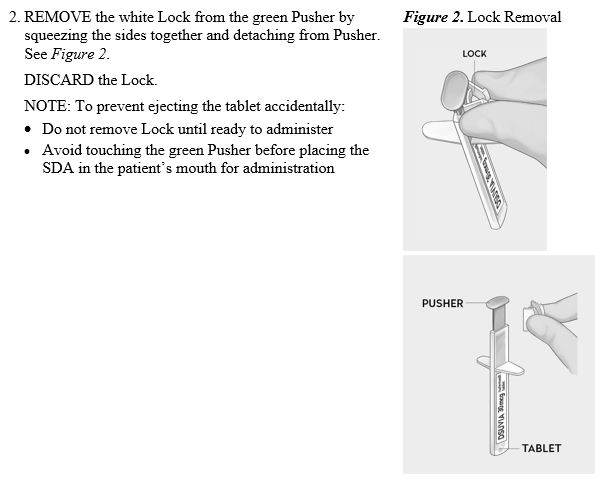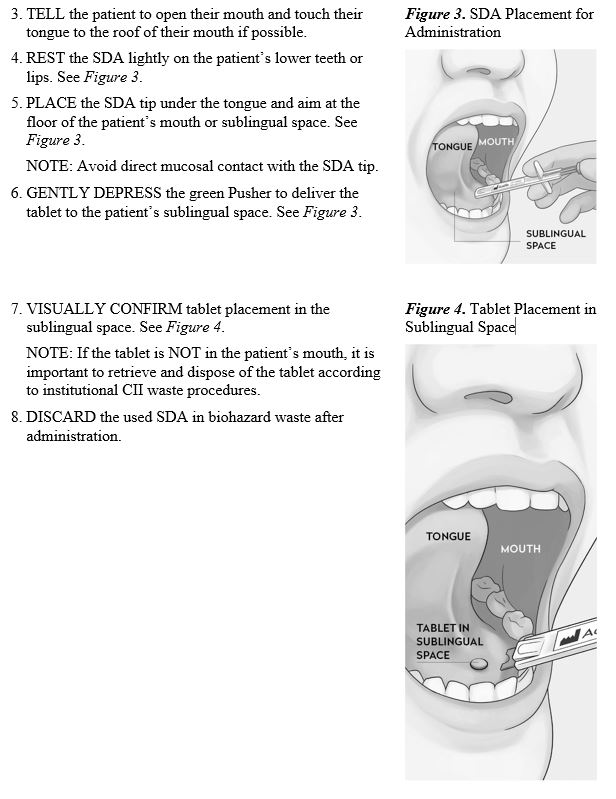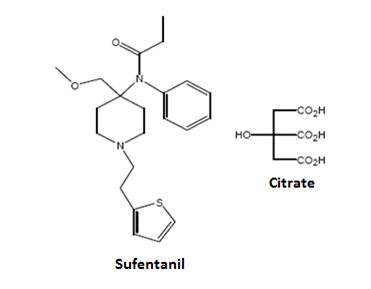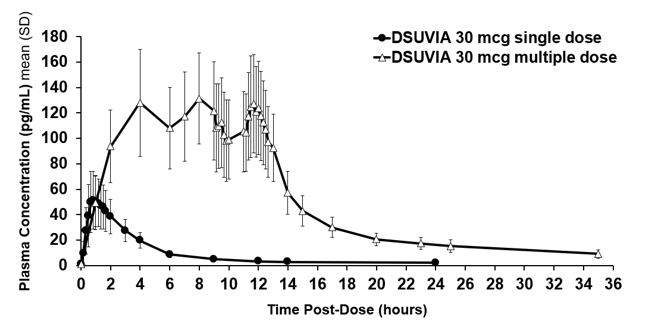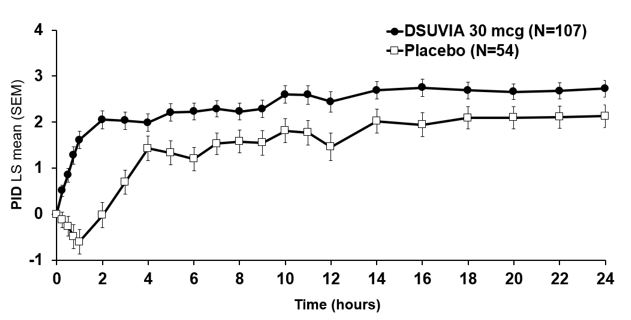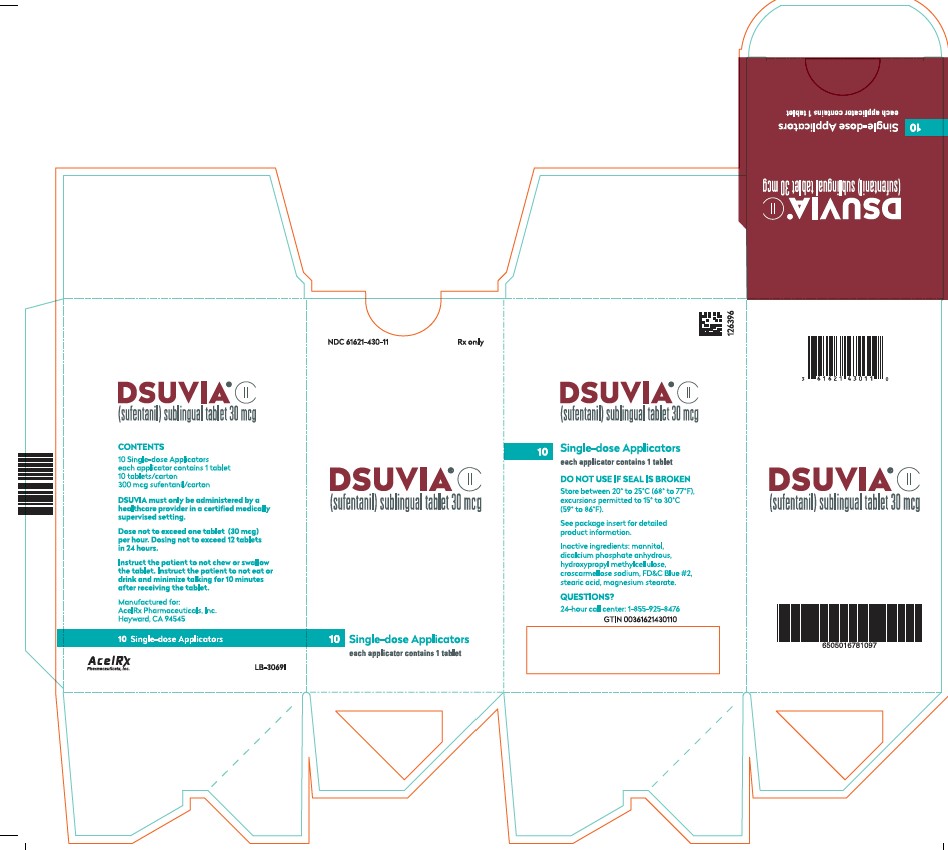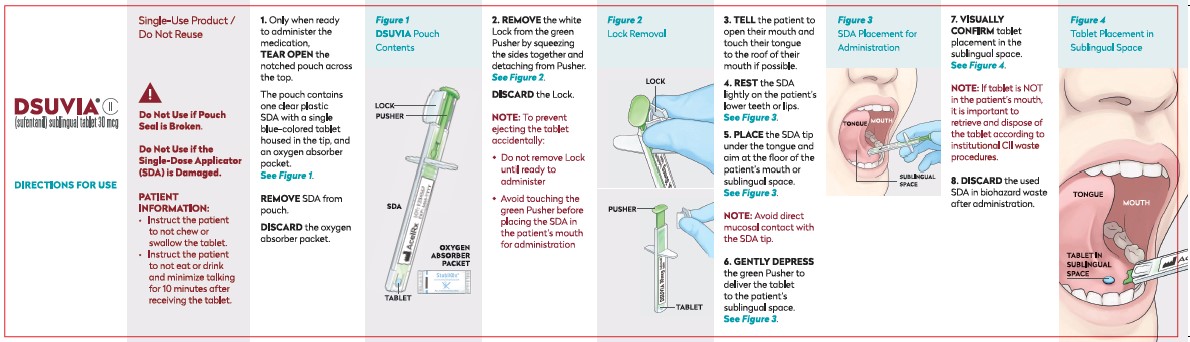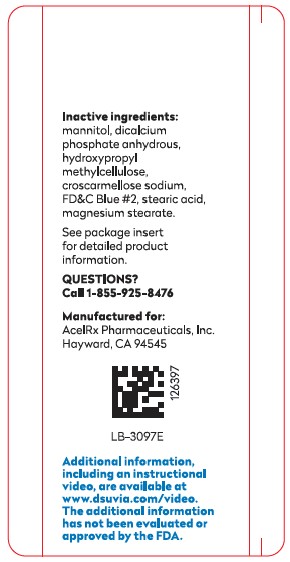 DRUG LABEL: Dsuvia
NDC: 61621-430 | Form: TABLET
Manufacturer: AcelRx Pharmaceuticals, Inc.
Category: prescription | Type: HUMAN PRESCRIPTION DRUG LABEL
Date: 20251230
DEA Schedule: CII

ACTIVE INGREDIENTS: SUFENTANIL 30 ug/1 1
INACTIVE INGREDIENTS: MANNITOL; CROSCARMELLOSE SODIUM; FD&C BLUE NO. 2; STEARIC ACID; MAGNESIUM STEARATE; ANHYDROUS DIBASIC CALCIUM PHOSPHATE; HYPROMELLOSE, UNSPECIFIED

HIGHLIGHTS OF PRESCRIBING INFORMATION

These highlights do not include all the information needed to use DSUVIA® safely and effectively. See full prescribing information for DSUVIA®.
DSUVIA® (sufentanil) sublingual tablet, CII
Initial U.S. Approval: 1984

RECENT MAJOR CHANGES

Indications and Usage (1) 12/2025

Warnings and Precautions (5.3, 5.4, 5.5, 5.13) 12/2025

WARNING: SERIOUS AND LIFE-THREATENING RISKS FROM USE OF DSUVIA

See full prescribing information for complete boxed warning.

- Accidental exposure to or ingestion of DSUVIA, especially in children, can result in respiratory depression and death.Because of the risk of life-threatening respiratory depression from accidental exposure, DSUVIA is available only through a restricted program called the DSUVIA REMS Program [see Warnings and Precautions (5.1, 5.2)]. DSUVIA should only be administered by a healthcare provider in a certified medically supervised healthcare setting. Discontinue use of DSUVIA prior to discharge or transfer from the certified medically supervised setting. (5.1, 5.2)
- DSUVIA exposes users to the risks of opioid addiction, abuse, and misuse, which can lead to overdose and death. Assess patient’s risk before prescribing, and reassess regularly for these behaviors and conditions. (5.3)
- Serious, life-threatening, or fatal respiratory depression may occur. Monitor closely, especially during initiation. (5.4)
- Concomitant use of opioids with benzodiazepines or other central nervous system (CNS) depressants, including alcohol, may result in profound sedation, respiratory depression, coma, and death. Reserve concomitant prescribing for use in patients for whom alternative treatment options are inadequate. (5.5, 7)
- Concomitant use with CYP3A4 inhibitors (or discontinuation of CYP3A4 inducers) can result in a fatal overdose of sufentanil. (5.6, 7, 12.3)

1 INDICATIONS AND USAGE

DSUVIA contains sufentanil, an opioid agonist, and is indicated for use in adults in a certified medically supervised healthcare setting, such as hospitals, surgical centers, and emergency departments, for the management of acute pain severe enough to require an opioid analgesic and for which alternative treatments are inadequate.

Limitations of Use:

- Not for home use or for use in children. Discontinue treatment with DSUVIA before patients leave the certified medically supervised healthcare setting. (1)
- Not for use for more than 72 hours.
- Only to be administered by a healthcare provider.
- Because of the risks of addiction, abuse, misuse, overdose, and death, which can occur at any dosage or duration and persist over the course of therapy, reserve opioid analgesics, including DSUVIA, for use in patients for whom alternative treatment options are ineffective, not tolerated, or would be otherwise inadequate to provide sufficient management of pain. (1, 5.3)

2 DOSAGE AND ADMINISTRATION

- Recommended dosage is 30 mcg sublingually as needed with a minimum of one hour between doses. (2.2)
- Use the lowest effective dosage for the shortest duration of time consistent with individual patient treatment goals. Reserve the use of additional doses of DSUVIA for patients in whom a single dose is insufficiently effective and in whom the expected benefits of using additional doses of an opioid clearly outweigh the substantial risks (2.2, 5).
- Respiratory depression can occur at any time during opioid therapy, especially when initiating and following additional doses of DSUVIA. Consider this risk when initiating dosing and when making dose adjustments (2.2, 5).
- Do not exceed 12 tablets in 24 hours. (2.2)
- See the Full Prescribing Information for administration information. (2.3)
- Do not rapidly reduce or abruptly discontinue DSUVIA in a physically-dependent patient. (9.3)

3 DOSAGE FORMS AND STRENGTHS

• Sublingual tablet: 30 mcg tablet housed in a disposable, single-dose applicator (SDA). (3)

4 CONTRAINDICATIONS

- Significant Respiratory Depression. (4)
- Acute or severe bronchial asthma in an unmonitored setting or in the absence of resuscitative equipment. (4)
- Known or suspected gastrointestinal obstruction, including paralytic ileus. (4)
- Known hypersensitivity to sufentanil or components of DSUVIA. (4)

5 WARNINGS AND PRECAUTIONS

- Opioid-Induced Hyperalgesia and Allodynia: Opioid-Induced Hyperalgesia (OIH) occurs when an opioid analgesic paradoxically causes an increase in pain, or an increase in sensitivity to pain. If OIH is suspected, carefully consider appropriately decreasing the dose of the current opioid analgesic, or opioid rotation. (5.7)
- Serotonin Syndrome: Potentially life-threatening condition could result from concomitant serotonergic drug administration. Discontinue DSUVIA if serotonin syndrome is suspected. (5.8)
- Life-Threatening Respiratory Depression in Patients with Chronic Pulmonary Disease or in Elderly, Cachectic, or Debilitated Patients: Monitor closely, particularly during initiation and titration. (5.9)
- Adrenal Insufficiency: If diagnosed, treat with physiologic replacement of corticosteroids, and wean patient off of the opioid. (5.10)
- Severe Hypotension: Monitor during dosage initiation and titration. Avoid use of DSUVIA in patients with circulatory shock. (5.11)
- Risks of Use in Patients with Increased Intracranial Pressure, Brain Tumors, Head Injury, or Impaired Consciousness: Monitor for sedation and respiratory depression. Avoid use of DSUVIA in patients with impaired consciousness or coma. (5.12)

6 ADVERSE REACTIONS

The most commonly reported adverse reactions (≥ 2%) were nausea, headache, vomiting, dizziness and hypotension. (6.1)

To report SUSPECTED ADVERSE REACTIONS, contact Vertical Pharmaceuticals, LLC at 1-855-925-8476 or FDA at 1-800-FDA-1088 or www.fda.gov/medwatch.

7 DRUG INTERACTIONS

• Mixed Agonist/Antagonist and Partial Agonist Opioid Analgesics: Avoid use with DSUVIA because they may reduce analgesic effect of DSUVIA or precipitate withdrawal symptoms. (7)

8 USE IN SPECIFIC POPULATIONS

• Hepatic and/or Renal Impairment: Monitor for signs of sedation and respiratory depression. (8.6, 8.7)

FULL PRESCRIBING INFORMATION

WARNING: SERIOUS AND LIFE-THREATENING RISKS FROM USE OF DSUVIA

Accidental Exposure and DSUVIA Risk Evaluation and Mitigation Strategy (REMS) Program

Accidental exposure to or ingestion of DSUVIA, especially in children, can result in respiratory depression and death. Because of the potential for life-threatening respiratory depression due to accidental exposure, DSUVIA is only available through a restricted program called the DSUVIA REMS Program [see Warnings and Precautions (5.1, 5.2)].

- DSUVIA must only be dispensed to patients in a certified medically supervised healthcare setting.
- Discontinue use of DSUVIA prior to discharge or transfer from the certified medically supervised healthcare setting.

Addiction, Abuse, and Misuse

Because the use of DSUVIA exposes patients and other users to the risks of opioid addiction, abuse, and misuse, which can lead to overdose and death, assess each patient’s risk prior to prescribing DSUVIA, and reassess all patients regularly for the development of these behaviors or conditions [see Warnings and Precautions (5.2)].

Life-Threatening Respiratory Depression

Serious, life-threatening, or fatal respiratory depression may occur with use of DSUVIA. Monitor for respiratory depression, especially during initiation of DSUVIA [see Warnings and Precautions (5.4)].

Risks From Concomitant Use With Benzodiazepines Or Other CNS Depressants

Concomitant use of opioids with benzodiazepines or other central nervous system (CNS) depressants, including alcohol, may result in profound sedation, respiratory depression, coma, and death. Reserve concomitant prescribing of DSUVIA and benzodiazepines or other CNS depressants for use in patients for whom alternative treatment options are inadequate [see Warnings and Precautions (5.5) and Drug Interactions (7)].

Cytochrome P450 3A4 Interaction

The concomitant use of DSUVIA with all cytochrome P450 3A4 inhibitors may result in an increase in sufentanil plasma concentrations, which could increase or prolong adverse drug reactions and may cause potentially fatal respiratory depression. In addition, discontinuation of a concomitantly used cytochrome P450 3A4 inducer may result in an increase in sufentanil plasma concentration. Monitor patients receiving DSUVIA and any CYP3A4 inhibitor or inducer [see Warnings and Precautions (5.6), Drug Interactions (7), and Clinical Pharmacology (12.3)].

1 INDICATIONS AND USAGE

DSUVIA is indicated for use in adults in a certified medically supervised healthcare setting, such as hospitals, surgical centers, and emergency departments, for the management of acute pain severe enough to require an opioid analgesic and for which alternative treatments are inadequate.

Limitations of Use:

- Not for home use or for use in children. Discontinue treatment with DSUVIA before patients leave the certified medically supervised healthcare setting.
- Not for use for more than 72 hours. The use of DSUVIA beyond 72 hours has not been studied.
- Only to be administered by a healthcare provider.
- Because of the risks of addiction, abuse, misuse, overdose, and death, which can occur at any dosage or duration and persist over the course of therapy, [see Warnings and Precautions (5.3)], reserve opioid analgesics, including DSUVIA, for use in patients for whom alternative treatment options are ineffective, not tolerated, or would be otherwise inadequate to provide sufficient management of pain.

2 DOSAGE AND ADMINISTRATION

2.1 Important Administration Instructions

DSUVIA is only to be administered by healthcare professionals who are knowledgeable about the use of opioids and how to mitigate the associated risks.

DSUVIA is only to be used in a certified medically supervised healthcare setting, such as hospitals, surgical centers, and emergency departments.

DSUVIA treatment must be discontinued prior to the patient leaving the certified medically supervised setting.

2.2 Dosage Information

The recommended dosage of DSUVIA is 30 mcg sublingually as needed with a minimum of 1 hour between doses. Do not exceed 12 tablets in 24 hours.

Use the lowest effective dosage for the shortest duration of time consistent with individual patient treatment goals [see Warnings and Precautions (5)]. Because the risk of overdose increases as opioid doses increase, reserve the use of additional doses of DSUVIA for patients in whom a single dose is insufficiently effective and in whom the expected benefits of using additional doses of an opioid clearly outweigh the substantial risks.

The maximum cumulative daily dose of sufentanil is 360 mcg or 12 tablets (12 tablets x 30 mcg/dose).

Initiate the dosing regimen for each patient individually, taking into account the patient’s underlying cause and severity of pain, prior analgesic treatment and response, and risk factors for addition, abuse, and misuse [see Warnings and Precautions (5.1)].

Respiratory depression can occur at any time during opioid therapy, especially when initiating and following additional doses of DSUVIA. Consider this risk when initiating dosing and when making dose adjustments [see Warnings and Precautions (5)].

2.3 Administration of DSUVIA

• Single-use product / Do not reuse.
• Do not use if pouch seal is broken.
• Do not use if the Single-Dose Applicator (SDA) is damaged.
• Wear gloves when administering DSUVIA.
• Instruct the patient to not chew or swallow the tablet.
• Instruct the patient to not eat or drink and minimize talking for 10 minutes after receiving the tablet. If a patient experiences excessive dry mouth, ice chips should be provided prior to administration of DSUVIA.
Administration Instructions

3 DOSAGE FORMS AND STRENGTHS

Sublingual tablets: DSUVIA is a single 30 mcg sufentanil tablet housed in a disposable, single-dose applicator (SDA). The tablet is blue-colored, flat-faced with rounded edges and is 3 mm in diameter.

4 CONTRAINDICATIONS

Use of DSUVIA is contraindicated in patients with:
• Significant respiratory depression [see Warnings and Precautions (5.4)]
• Acute or severe bronchial asthma in an unmonitored setting or in the absence of resuscitative equipment [see Warnings and Precautions (5.9)]
• Known or suspected gastrointestinal obstruction, including paralytic ileus [see Warnings and Precautions (5.13)]
• Known hypersensitivity to sufentanil or components of DSUVIA [see Adverse Reactions (6.1, 6.2)].

5 WARNINGS AND PRECAUTIONS

5.1 Risk of Respiratory Depression and Death Due to Accidental Exposure

Accidental ingestion or exposure to even one dose of DSUVIA, especially in children, can result in respiratory depression and death due to an overdose of sufentanil.

DSUVIA is for use in adult patients only in a certified medically supervised healthcare setting. Use of DSUVIA outside of this setting can increase the risk of accidental exposure in others for whom it is not prescribed, causing fatal respiratory depression. Discontinue use of DSUVIA prior to discharge or transfer from the certified medically supervised healthcare setting. DSUVIA is not for home or pediatric use.

Following accidental ingestion of DSUVIA, monitor patients for opioid-related adverse events, such as respiratory depression.

5.2 DSUVIA Risk Evaluation and Mitigation Strategy (REMS)

Because of the potential for life-threatening respiratory depression due to accidental exposure, DSUVIA is only available through a restricted program under a Risk Evaluation and Mitigation Strategy (REMS) called the DSUVIA REMS Program.

The goal of the DSUVIA REMS is to mitigate the risk of respiratory depression resulting from accidental exposure by:
• Ensuring that DSUVIA is dispensed only to patients in certified medically supervised healthcare settings.

The requirements of the DSUVIA REMS are as follows:

• Healthcare settings that dispense DSUVIA must:
- Be able to manage an acute opioid overdose including respiratory depression
- Train all relevant staff that DSUVIA must not be dispensed for use outside of the certified healthcare setting
- Train all relevant staff involved in administration of DSUVIA to refer to the Directions for Use prior to administration
- Establish processes and procedures to verify that DSUVIA is not dispensed for use outside of the certified healthcare setting.

• Wholesalers that distribute DSUVIA must:
- Establish processes and procedures to ensure that DSUVIA is distributed only to certified medically supervised healthcare settings.
- Distribute only to certified medically supervised healthcare settings.

Further information about the DSUVIA REMS Program is available at www.DSUVIAREMS.com, or by calling 1-855-925-8476.

5.3 Addiction, Abuse and Misuse

DSUVIA contains sufentanil, a Schedule II controlled substance. As an opioid, DSUVIA exposes users to the risks of addiction, abuse, and misuse [see Drug Abuse and Dependence (9)].

Although the risk of addiction in any individual is unknown, it can occur in patients appropriately prescribed DSUVIA. Addiction can occur at recommended dosages and if the drug is misused or abused. The risk of opioid-related overdose or overdose-related death is increased with higher opioid doses, and this risk persists over the course of therapy. In postmarketing studies, addiction, abuse, misuse, and fatal and non-fatal opioid overdose were observed in patients with long-term opioid use [see Adverse Reactions (6.2)].

Assess each patient’s risk for opioid addiction, abuse, or misuse prior to prescribing DSUVIA, and monitor all patients receiving DSUVIA for the development of these behaviors or conditions. Risks are increased in patients with a personal or family history of substance abuse (including drug or alcohol abuse or addiction) or mental illness (e.g., major depression). The potential for these risks should not, however, prevent the proper management of pain in any given patient. Patients at increased risk may be prescribed opioids such as DSUVIA but use in such patients necessitates intensive counseling about the risks and proper use of DSUVIA along with intensive monitoring for signs of addiction, abuse, and misuse.

Opioids are sought for nonmedical use and are subject to diversion from legitimate prescribed use. Consider these risks when prescribing or dispensing DSUVIA. Strategies to reduce these risks include proper product storage and control practices for a C-II drug. Contact local state professional licensing board or state-controlled substances authority for information on how to prevent and detect abuse or diversion of this product.

5.4 Life-Threatening Respiratory Depression

Serious, life-threatening, or fatal respiratory depression has been reported with the use of opioids, even when used as recommended. Respiratory depression, if not immediately recognized and treated, may lead to respiratory arrest and death. Management of respiratory depression may include close observation, supportive measures, and use of opioid overdose reversal agents (e.g., naloxone, nalmefene), depending on the patient’s clinical status [see Overdosage (10)]. Carbon dioxide (CO2) retention from opioid-induced respiratory depression can exacerbate the sedating effects of opioids.

While serious, life-threatening, or fatal respiratory depression can occur at any time during the use of DSUVIA, the risk is greatest during the initiation of therapy. Monitor patients closely for respiratory depression while on treatment with DSUVIA.

Accidental exposure to or ingestion of even one dose of DSUVIA, especially in children, can result in respiratory depression and death due to an overdose of sufentanil.

Opioids can cause sleep-related breathing disorders including central sleep apnea (CSA) and sleep-related hypoxemia. Opioid use increases the risk of CSA in a dose-dependent fashion. In patients who present with CSA, consider minimizing the use of DSUVIA and carefully monitor the patient for signs of respiratory depression [see Dosage and Administration (2.2)].

5.5 Risks from Concomitant Use with Benzodiazepines or other CNS Depressants

Profound sedation, respiratory depression, coma, and death may result from the concomitant use of DSUVIA with benzodiazepines or other CNS depressants, including alcohol (e.g., non-benzodiazepine sedatives/hypnotics, anxiolytics, tranquilizers, muscle relaxants, general anesthetics, antipsychotics, gabapentinoids [gabapentin or pregabalin], and other opioids). Because of these risks, reserve concomitant prescribing of these drugs for use in patients for whom alternative treatment options are inadequate. Monitor patients closely for signs and symptoms of respiratory depression and sedation.

Observational studies have demonstrated that concomitant use of opioid analgesics and benzodiazepines increases the risk of drug-related mortality compared to use of opioid analgesics alone. Because of similar pharmacological properties, it is reasonable to expect similar risk with the concomitant use of other CNS depressant drugs with opioid analgesics [see Drug Interactions (7)].

If the decision is made to prescribe a benzodiazepine or other CNS depressant concomitantly with an opioid analgesic, prescribe the lowest effective dosages and minimum durations of concomitant use. In patients already receiving an opioid analgesic, prescribe a lower initial dose of the benzodiazepine or other CNS depressant than indicated in the absence of an opioid, and titrate based on clinical response. If an opioid analgesic is initiated in a patient already taking a benzodiazepine or other CNS depressant, prescribe a lower initial dose of the opioid analgesic, and titrate based on clinical response. Follow patients closely for signs and symptoms of respiratory depression and sedation.

5.6 Risks of Concomitant Use or Discontinuation of Cytochrome P450 3A4 Inhibitors and Inducers

Concomitant use of DSUVIA with a CYP3A4 inhibitor, such as macrolide antibiotics (e.g. erythromycin), azole-antifungal agents (e.g., ketoconazole), and protease inhibitors (e.g., ritonavir), may increase plasma concentrations of sufentanil and prolong opioid adverse reactions, which may cause potentially fatal respiratory depression [see Warnings and Precautions (5.4)], particularly when an inhibitor is added after a stable dose of DSUVIA is achieved. Similarly, discontinuation of a CYP3A4 inducer, such as rifampin, carbamazepine, and phenytoin, in DSUVIA-treated patients may increase sufentanil plasma concentrations and prolong opioid adverse reactions. When using DSUVIA with CYP3A4 inhibitors or discontinuing CYP3A4 inducers in DSUVIA-treated patients, monitor patients closely at frequent intervals for respiratory depression and sedation [see Drug Interactions (7)].

Concomitant use of DSUVIA with CYP3A4 inducers or discontinuation of a CYP3A4 inhibitor could decrease sufentanil plasma concentrations, decrease opioid efficacy or, possibly lead to a withdrawal syndrome in a patient who had developed physical dependence to sufentanil. When using DSUVIA with CYP3A4 inducers or discontinuing CYP3A4 inhibitors, monitor patients closely at frequent intervals for adequate analgesia and for symptoms of opioid withdrawal [see Drug Interactions (7)].

5.7 Opioid-Induced Hyperalgesia and Allodynia

Opioid-Induced Hyperalgesia (OIH) occurs when an opioid analgesic paradoxically causes an increase in pain, or an increase in sensitivity to pain. This condition differs from tolerance, which is the need for increasing doses of opioids to maintain a defined effect [see Dependence (9.3)]. Symptoms of OIH include (but may not be limited to) increased levels of pain upon opioid dosage increase, decreased levels of pain upon opioid dosage decrease, or pain from ordinarily non-painful stimuli (allodynia). These symptoms may suggest OIH only if there is no evidence of underlying disease progression, opioid tolerance, opioid withdrawal, or addictive behavior.

Cases of OIH have been reported, both with short-term and longer-term use of opioid analgesics. Though the mechanism of OIH is not fully understood, multiple biochemical pathways have been implicated. Medical literature suggests a strong biologic plausibility between opioid analgesics and OIH and allodynia. If a patient is suspected to be experiencing OIH, carefully consider appropriately decreasing the dose of the current opioid analgesic, or opioid rotation (safely switching the patient to a different opioid moiety).

5.8 Serotonin Syndrome with Concomitant Use of Serotonergic Drugs

Cases of serotonin syndrome, a potentially life-threatening condition, have been reported during concomitant use of sufentanil, the active opioid ingredient of DSUVIA, with serotonergic drugs. Serotonergic drugs include selective serotonin reuptake inhibitors (SSRIs), serotonin and norepinephrine reuptake inhibitors (SNRIs), tricyclic antidepressants (TCAs), triptans, 5-HT3 receptor antagonists, drugs that affect the serotonergic neurotransmitter system (e.g., mirtazapine, trazodone, tramadol), certain muscle relaxants (e.g., cyclobenzaprine, metaxalone), and drugs that impair metabolism of serotonin (including MAO inhibitors, both those intended to treat psychiatric disorders and also others, such as linezolid and intravenous methylene blue) [see Drug Interactions (7)]. This may occur at the recommended dosage.

Serotonin syndrome symptoms may include mental status changes (e.g., agitation, hallucinations, coma), autonomic instability (e.g., tachycardia, labile blood pressure, hyperthermia), neuromuscular aberrations (e.g., hyperreflexia, incoordination, rigidity), and/or gastrointestinal symptoms (e.g., nausea, vomiting, diarrhea) and can be fatal. The onset of symptoms generally occurs within several hours to a few days of concomitant use, but may occur later than that. Discontinue DSUVIA if serotonin syndrome is suspected.

5.9 Life-Threatening Respiratory Depression in Patients with Chronic Pulmonary Disease or in Elderly, Cachectic, or Debilitated Patients

The use of DSUVIA in patients with acute or severe bronchial asthma in an unmonitored setting or in the absence of resuscitative equipment is contraindicated.

Patients with Chronic Pulmonary Disease: DSUVIA-treated patients with significant chronic obstructive pulmonary disease or cor pulmonale, and those with a substantially decreased respiratory reserve, hypoxia, hypercapnia, or pre-existing respiratory depression are at increased risk of decreased respiratory drive including apnea, even at the recommended dosage of DSUVIA [see Warnings and Precautions (5.4)].

Elderly, Cachectic, or Debilitated Patients: Life-threatening respiratory depression is more likely to occur in elderly, cachectic, or debilitated patients as they may have altered pharmacokinetics or altered clearance compared to younger, healthier patients.

Monitor such patients closely; particularly when initiating DSUVIA and when DSUVIA is used concomitantly with other drugs that depress respiration [see Warnings and Precautions (5.4)]. Alternatively, consider the use of non-opioid analgesics in these patients.

5.10 Adrenal Insufficiency

Cases of adrenal insufficiency have been reported with opioid use, more often following greater than one month of use. Presentation of adrenal insufficiency may include non-specific symptoms and signs including nausea, vomiting, anorexia, fatigue, weakness, dizziness, and low blood pressure. If adrenal insufficiency is suspected, confirm the diagnosis with diagnostic testing as soon as possible. If adrenal insufficiency is diagnosed, treat with physiologic replacement doses of corticosteroids. Wean the patient off the opioid to allow adrenal function to recover and continue corticosteroid treatment until adrenal function recovers. Other opioids may be tried as some cases reported use of a different opioid without recurrence of adrenal insufficiency. The information available does not identify any particular opioids as being more likely to be associated with adrenal insufficiency.

5.11 Severe Hypotension

DSUVIA may cause severe hypotension, including orthostatic hypotension and syncope in ambulatory patients. There is an increased risk in patients whose ability to maintain blood pressure has already been compromised by a reduced blood volume or concurrent administration of certain CNS depressant drugs (e.g., phenothiazines or general anesthetics) [see Drug Interactions (7)]. Monitor these patients for signs of hypotension after initiating DSUVIA. In patients with circulatory shock, DSUVIA may cause vasodilation that can further reduce cardiac output and blood pressure. Avoid the use of DSUVIA in patients with circulatory shock.

5.12 Risks of Use in Patients with Increased Intracranial Pressure, Brain Tumors, Head Injury, or Impaired Consciousness

In patients who may be susceptible to the intracranial effects of CO2 retention (e.g., those with evidence of increased intracranial pressure or brain tumors), DSUVIA may reduce respiratory drive, and the resultant CO2 retention can further increase intracranial pressure. Monitor such patients for signs of sedation and respiratory depression, particularly when initiating therapy with DSUVIA.

Opioids may also obscure the clinical course in a patient with a head injury. Avoid the use of DSUVIA in patients with impaired consciousness or coma. DSUVIA is not suitable for use in patients who are not alert and able to follow directions.

5.13 Risks of Gastrointestinal Complications

DSUVIA is contraindicated in patients with known or suspected gastrointestinal obstruction, including paralytic ileus.

The sufentanil in DSUVIA may cause spasm of the sphincter of Oddi. Opioids may cause increases in serum amylase. Monitor patients with biliary tract disease, including acute pancreatitis for worsening symptoms.

Cases of opioid-induced esophageal dysfunction (OIED) have been reported in patients taking opioids. The risk of OIED may increase as the dose and/or duration of opioids increases. Regularly evaluate patients for signs and symptoms of OIED (e.g. dysphagia, regurgitation, non-cardiac chest pain), and if necessary, adjust opioid therapy as clinically appropriate [see Clinical Pharmacology (12.2)].

5.14 Increased Risk of Seizures in Patients with Seizure Disorders

The sufentanil in DSUVIA may increase the frequency of seizures in patients with seizure disorders, and may increase the risk of seizures occurring in other clinical settings associated with seizures. Monitor patients with a history of seizure disorders for worsened seizure control during DSUVIA therapy.

5.15 Bradycardia

DSUVIA may produce bradycardia in some patients. Monitor patients with bradyarrhythmias closely for changes in heart rate, particularly when initiating therapy with DSUVIA.

5.16 Neonatal Opioid Withdrawal Syndrome

Use of opioids for an extended period of time during pregnancy can result in withdrawal in the neonate. Neonatal opioid withdrawal syndrome, unlike opioid withdrawal syndrome in adults, may be life-threatening if not recognized and treated, and requires management according to protocols developed by neonatology experts. Observe newborns for signs of neonatal opioid withdrawal syndrome and manage accordingly. Advise pregnant women using opioids for an extended period of time of the risk of neonatal opioid withdrawal syndrome and ensure that appropriate treatment will be available [see Use in Specific Populations (8.1)].

6 ADVERSE REACTIONS

The following serious adverse reactions are described, or described in greater detail, in other sections:

- Addiction, Abuse, and Misuse [see Warnings and Precautions (5.3)]
- Life-Threatening Respiratory Depression [see Warnings and Precautions (5.4)]
- Opioid-Induced Hyperalgesia and Allodynia [see Warnings and Precautions (5.7)]
- Adrenal Insufficiency [see Warnings and Precautions (5.10)]
- Severe Hypotension [see Warnings and Precautions (5.11)]
- Gastrointestinal Adverse Reactions [see Warnings and Precautions (5.13)]
- Seizures [see Warnings and Precautions (5.14)]
- Neonatal Opioid Withdrawal Syndrome [see Warnings and Precautions (5.16)]

6.1 Clinical Trials Experience

Because clinical trials are conducted under widely varying conditions, adverse reaction rates observed in the clinical trials of a drug cannot be directly compared to rates in the clinical trials of another drug and may not reflect the rates observed in clinical practice.
In controlled and uncontrolled studies, the safety of DSUVIA was evaluated in a total of 646 patients with moderate-to-severe acute postoperative pain or pain due to trauma which required opioid analgesia.
The most frequently reported adverse reactions ≥ 2% that were probably or possibly related to study treatment in the one pivotal, placebo-controlled trial (Study SAP301) are presented in Table 1.
Discontinuation of study drug due to adverse events occurred in 0.9% of DSUVIA-treated patients (1 out of 107 patients) and 3.7% of placebo-treated patients (2 out of 54 placebo treated patients). The most common reasons for discontinuation of study drug due to adverse reactions in SAP301 were oxygen saturation decreased (0.9% in the DSUVIA group), and dizziness, hemiparesis, somnolence and syncope in the placebo group (1.9% each).
Table 1: Adverse Reactions Occurring in ≥ 2% of Patients and for Which Rate is Higher in DSUVIA than Placebo Group: Placebo-Controlled Study SAP301

Possibly or Probably Related Adverse Reactions | DSUVIA n=107 | Placebo * n=54
Nausea | 29.0% | 22.2%
Headache | 12.1% | 11.1%
Vomiting | 5.6% | 1.9%
Dizziness | 5.6% | 3.7%
Hypotension | 4.7% | 3.7%

*Morphine 1 mg IV was permitted as rescue medication

Other Reported Adverse Reactions
Additional treatment related adverse drug reactions which occurred in at least 0.1% of the patients exposed to 30 mcg or higher of sublingual sufentanil are described below.
Cardiac Disorders: sinus tachycardia, bradycardia.
Gastrointestinal Disorders: constipation, dyspepsia, flatulence, diarrhea, dry mouth, eructation, retching, abdominal discomfort, abdominal distension, abdominal pain upper, gastritis, postoperative ileus, hypoesthesia oral.
Investigations: oxygen saturation decreased, respiratory rate decreased, urine output decreased, aspartate aminotransferase increased, electrocardiogram abnormal, hepatic enzyme increased.
Musculoskeletal and Connective Tissue Disorders: muscle spasms.
Nervous System Disorders: somnolence, sedation, presyncope, lethargy, memory impairment.
Psychiatric Disorders: insomnia, confusional state, anxiety, agitation, disorientation, euphoric mood, hallucination, mental status changes.
Renal and Urinary Disorders: urinary retention, urinary hesitation, oliguria, renal failure.
Respiratory, Thoracic and Mediastinal Disorders: hypoxia, bradypnea, hiccups, apnea, atelectasis, hypoventilation, respiratory distress, respiratory failure.
Skin and Subcutaneous Tissue Disorders: pruritus, hyperhidrosis, rash.
Vascular Disorders: hypotension, hypertension, orthostatic hypotension, flushing.

6.2 Postmarketing Experience

The following adverse reactions have been identified during post-approval use of sufentanil. Because these reactions are reported voluntarily from a population of uncertain size, it is not always possible to reliably estimate their frequency or establish a causal relationship to drug exposure.

Serotonin syndrome: Cases of serotonin syndrome, a potentially life-threatening condition, have been reported during concomitant use of opioids with serotonergic drugs.

Adrenal insufficiency: Cases of adrenal insufficiency have been reported with opioid use, more often following greater than one month of use.

Anaphylaxis: Anaphylaxis has been reported with ingredients contained in DSUVIA.

Androgen deficiency: Cases of androgen deficiency have occurred with use of opioids for an extended period of time.

Hyperalgesia and Allodynia: Cases of hyperalgesia and allodynia have been reported with opioid therapy of any duration [see Warnings and Precautions (5.7)].

Hypoglycemia: Cases of hypoglycemia have been reported in patients taking opioids. Most reports were in patients with at least one predisposing risk factor (e.g., diabetes).

Opioid-induced esophageal dysfunction (OIED): Cases of OIED have been reported in patients taking opioids, and may occur more frequently in patients taking higher doses of opioids, and/or in patients taking opioids longer term [see Warnings and Precautions (5.13)].

Adverse Reactions from Observational Studies

A prospective, observational cohort study estimated the risks of addiction, abuse, misuse in patients initiating long-term use of Schedule II opioid analgesics between 2017 and 2021. Study participants included in one or more analyses had been enrolled in selected insurance plans or health systems for at least one year, were free of at least one outcome at baseline, completed a minimum number of follow-up assessments, and either: 1) filled multiple extended-release/long acting opioid analgesic prescriptions during a 90-day period (n=978); or 2) filled any Schedule II opioid analgesic prescriptions covering at least 70 of 90 days (n=1,244). Those included also had no dispensing of the qualifying opioids in the previous 6 months.

Over 12 months:

- approximately 15 to 6% of participants across the two cohorts newly meet criteria for addiction, as assessed with two validated interview-based measures of moderate-to-sever opioid use disorder based on Diagnostic and Statistical Manual of Mental Disorders, Fifth Edition (DSM-5) criteria, and
- approximately 9% and 22% of participants across the two cohorts newly met criteria for prescription opioid abuse and misuse [defined in Drug Abuse and Dependence (9.2)], respectively, as measured with a validated self-reported instrument.

A retrospective, observational cohort study estimated the risk of opioid involved overdose or opioid overdose-related death in patients with new long-term use of Schedule II opioid analgesics from 2006 through 2016 (n=220,249). Included patients had been enrolled in either one of two commercial insurance programs, one managed care program, or one Medicaid program for at least 9 months. New long-term use was defined as having Schedule II opioid analgesic prescriptions covering at least 70 days’ supply over the 3 months prior to study entry and none during the preceding 6 months. Patients were excluded if they had an opioid-involved overdose in the 9 months prior to study entry. Overdose was measured using a validated medical code-based algorithm with linkage to the National Death Index database. The 5-year cumulative incidence estimates for opioid-involved overdose or opioid overdose-related death ranged from approximately 1.5% to 4% across study sites, counting only the first event during follow-up. Approximately 17% of first opioid overdoses observed over the entire study period (5-11 years, depending on the study site) were fatal. Higher baseline opioid dose was the strongest and most consistent predictor of opioid-involved overdose or opioid overdose-related death. Study exclusion criteria may have selected patients at lower risk of overdose, and substantial loss to follow-up (approximately 80%) also may have biased estimates.

The risk estimates from the studies described above may not be generalizable to all patients receiving opioid analgesics, such as those with exposures shorter or longer than the duration evaluated in the studies.

7 DRUG INTERACTIONS

Table 2 includes clinically significant drug interactions with DSUVIA.
Table 2: Clinically Significant Drug Interactions with DSUVIA

Inhibitors of CYP3A4
Clinical Impact: | The concomitant use of DSUVIA and CYP3A4 inhibitors can increase the plasma concentration of sufentanil, resulting in increased or prolonged opioid effects. After stopping a CYP3A4 inhibitor, as the effects of the inhibitor decline, the sufentanil plasma concentration will decrease [see Clinical Pharmacology (12.3)], resulting in decreased opioid efficacy or a withdrawal syndrome in patients who had developed physical dependence to sufentanil.
Intervention: | If concomitant use is necessary, consider an alternate medication that permits dose titration. Monitor patients for respiratory depression and sedation at frequent intervals. If a CYP3A4 inhibitor is discontinued, consider an alternate medication that permits dose titration. Monitor for signs of opioid withdrawal.
Examples: | Macrolide antibiotics (e.g., erythromycin), azole-antifungal agents (e.g. ketoconazole), protease inhibitors (e.g., ritonavir)
CYP3A4 Inducers
Clinical Impact: | The concomitant use of DSUVIA and CYP3A4 inducers can decrease the plasma concentration of sufentanil [see Clinical Pharmacology (12.3)], resulting in decreased efficacy or onset of a withdrawal syndrome in patients who have developed physical dependence to sufentanil [see Warnings and Precautions (5.6)]. After stopping a CYP3A4 inducer, as the effects of the inducer decline, the sufentanil plasma concentration will increase [see Clinical Pharmacology (12.3)], which could increase or prolong both the therapeutic effects and adverse reactions, and may cause serious respiratory depression.
Intervention: | If concomitant use is necessary, consider an alternate medication that permits dose titration. Monitor for signs of opioid withdrawal. If a CYP3A4 inducer is discontinued, consider less frequent dosing of DSUVIA and monitor for signs of respiratory depression.
Examples: | Rifampin, carbamazepine, phenytoin
Benzodiazepines and other Central Nervous System (CNS) Depressants
Clinical Impact: | Due to additive pharmacologic effect, the concomitant use of benzodiazepines or CNS depressants, including alcohol, can increase the risk of hypotension, respiratory depression, profound sedation, coma, and death [see Warnings and Precautions (5.5)].
Intervention: | Reserve concomitant prescribing of these drugs for use in patients for whom alternative treatment options are inadequate. Limit dosages and durations to the minimum required. Follow patients closely for signs of respiratory depression and sedation [see Warnings and Precautions (5.5)].
Examples: | Alcohol, benzodiazepines and other sedatives/hypnotics, anxiolytics, tranquilizers, muscle relaxants, general anesthetics, antipsychotics, gabapentinoids (gabapentin or pregabalin), other opioids.
Serotonergic Drugs
Clinical Impact: | The concomitant use of opioids with other drugs that affect the serotonergic neurotransmitter system has resulted in serotonin syndrome [see Warnings and Precautions (5.8)].
Intervention: | If concomitant use is warranted, carefully observe the patient, particularly during treatment initiation and dose adjustment. Discontinue DSUVIA if serotonin syndrome is suspected.
Examples: | Selective serotonin reuptake inhibitors (SSRIs), serotonin and norepinephrine reuptake inhibitors (SNRIs), tricyclic antidepressants (TCAs), triptans, 5-HT3 receptor antagonists, drugs that effect the serotonin neurotransmitter system (e.g., mirtazapine, trazodone, tramadol), certain muscle relaxants (e.g., cyclobenzaprine, metaxalone), monoamine oxidase (MAO) inhibitors (those intended to treat psychiatric disorders and also others, such as linezolid and intravenous methylene blue).
Monoamine Oxidase Inhibitors (MAOIs)
Clinical Impact: | MAOI interactions with opioids may manifest as serotonin syndrome or opioid toxicity (e.g., respiratory depression, coma) [see Warnings and Precautions (5.4)].
Intervention: | The use of DSUVIA is not recommended for patients taking MAOIs or within 14 days of stopping such treatment.
Examples: | phenelzine, tranylcypromine, linezolid
Mixed Agonist/Antagonist and Partial Agonist Opioid Analgesics
Clinical Impact: | May reduce the analgesic effect of DSUVIA and/or precipitate withdrawal symptoms.
Intervention: | Avoid concomitant use.
Examples: | Butorphanol, nalbuphine, pentazocine, buprenorphine
Muscle Relaxants
Clinical Impact: | Sufentanil may enhance the neuromuscular blocking action of skeletal muscle relaxants and produce an increased degree of respiratory depression.
Intervention: | Because respiratory depression may be greater than otherwise expected, decrease the dosage of the muscle relaxant as necessary or consider discontinuing use of DSUVIA.
Examples: | Cyclobenzaprine, metaxolone.
Diuretics
Clinical Impact: | Opioids can reduce the efficacy of diuretics by inducing the release of antidiuretic hormone.
Intervention: | Monitor patients for signs of diminished diuresis and/or effects on blood pressure and increase the dosage of the diuretic as needed.
Anticholinergic Drugs
Clinical Impact: | The concomitant use of anticholinergic drugs may increase risk of urinary retention and/or severe constipation, which may lead to paralytic ileus.
Intervention: | Monitor patients for signs of urinary retention or reduced gastric motility when DSUVIA is used concomitantly with anticholinergic drugs.

8 USE IN SPECIFIC POPULATIONS

8.1 Pregnancy

Risk Summary

Use of opioid analgesics for an extended period of time during pregnancy may cause neonatal opioid withdrawal syndrome [see Warnings and Precautions (5.16)]. There are no available data with sufentanil in pregnant women to inform a drug-associated risk for major birth defects and miscarriage.

In animal reproduction studies, embryolethality and maternal toxicity were noted in rabbits when sufentanil was administered intravenously at 4.4 times the maximum human daily dose of 360 mcg/60 kg/day, based on a body surface area comparison during organogenesis. Decreased live fetuses and pup survival were noted in rats treated with sufentanil late in gestation and throughout lactation at doses below the human daily dose of 360 mcg. No malformations were observed in either rats or rabbits at doses below the human daily dose of 360 mcg [see Data].

The background risk of major birth defects and miscarriage for the indicated population is unknown. All pregnancies have a background risk of birth defect, loss, or other adverse outcomes. In the U.S. general population, the estimated background risk of major birth defects and miscarriage in clinically recognized pregnancies is 2 to 4% and 15 to 20%, respectively.

Clinical Considerations

Fetal/Neonatal Adverse Reactions

Use of opioid analgesics for an extended period of time during pregnancy for medical or non-medical purposes can result in physical dependence in the neonate and neonatal opioid withdrawal syndrome shortly after birth.

Neonatal opioid withdrawal syndrome presents as irritability, hyperactivity and abnormal sleep pattern, high pitched cry, tremor, vomiting, diarrhea and failure to gain weight. The onset, duration, and severity of neonatal opioid withdrawal syndrome vary based on the specific opioid used, duration of use, timing and amount of last maternal use, and rate of elimination of the drug by the newborn. Observe newborns for symptoms of neonatal opioid withdrawal syndrome and manage accordingly [see Warnings and Precautions (5.16)].

Labor or Delivery

Opioids cross the placenta and may produce respiratory depression and psycho-physiologic effects in neonates. An opioid overdose reversal agent, such as naloxone or nalmefene, must be available for reversal of opioid-induced respiratory depression in the neonate. DSUVIA is not recommended for use in pregnant women during or immediately prior to labor, when other analgesic techniques are more appropriate. Opioid analgesics, including DSUVIA, can prolong labor through actions which temporarily reduce the strength, duration, and frequency of uterine contractions. However, this effect is not consistent and may be offset by an increased rate of cervical dilation, which tends to shorten labor. Monitor neonates exposed to opioid analgesics during labor for signs of excess sedation and respiratory depression.

Data

Animal Data

Pregnant rats were treated with intravenous sufentanil doses of 0.005, 0.02, or 0.08 mg/kg/day (0.14, 0.6, or 2.2 times the maximum human daily dose of 360 mcg/60 kg, based on body surface area, respectively). No malformations or embryotoxic effects were noted despite maternal toxicity (increased mortality in the mid- and high-dose group).

Pregnant rabbits were treated with intravenous sufentanil doses of 0.005, 0.02, or 0.08 mg/kg/day (0.2, 1.0, or 4.4 times the maximum human daily dose of 360 mcg/60 kg, based on body surface area, respectively). Decreased live fetuses per litter and decreased litter size in the high dose group were noted in the presence of maternal toxicity (decreased body weight gain and mortality in the high-dose group).

No evidence of malformations or adverse effects on the fetus was reported in a published study in which pregnant rats were administered 10, 50, or 100 mcg/kg/day sufentanil (0.2, 1.4, or 2.8 times the maximum human daily dose of 360 mcg/60 kg, based on body surface area) continuously from Gestation Day 5 through Gestation Day 20 via subcutaneously implanted osmotic minipumps.

Pregnant rats were treated intravenously with sufentanil 0.005, 0.02, or 0.08 mg/kg/day (0.14, 0.6, or 2.2 times the maximum human daily dose of 360 mcg/60 kg, based on body surface area, respectively) from Gestation Day 16 through Lactation Day 21. Sufentanil reduced birth weights in the mid- and high-dose groups, decreased live fetuses in the high-dose group, and decreased pup survival in all groups in the presence of maternal toxicity (decreased weight gain and increased mortality in all groups).

8.2 Lactation

Risk Summary

The developmental and health benefits of breastfeeding should be considered along with the mother’s clinical need for DSUVIA and any potential adverse effects on the breastfed infant from DSUVIA or from the underlying maternal condition.

Clinical Considerations

Monitor infants exposed to DSUVIA through breast milk for excess sedation and respiratory depression. Withdrawal symptoms can occur in breastfed infants when maternal administration of an opioid analgesic is stopped, or when breast-feeding is stopped.

8.3 Females and Males of Reproductive Potential

Infertility

Use of opioids for an extended period of time may cause reduced fertility in females and males of reproductive potential. It is not known whether these effects on fertility are reversible. DSUVIA is not intended for chronic use [see Adverse Reactions (6.2), Clinical Pharmacology (12.2), Nonclinical Toxicology (13.1)].

8.4 Pediatric Use

The safety and efficacy of the use of DSUVIA in pediatric patients has not been established.
The ability of pediatric patients to comply with the sublingual dosing instructions for DSUVIA has not been evaluated. Use of DSUVIA in younger children is not recommended as younger children may not be able to comply with the sublingual dosing instructions for DSUVIA and could swallow the tablet or spit it out, which could impact the efficacy and safety of DSUVIA.

8.5 Geriatric Use

No special population studies were performed using DSUVIA in elderly patients.

Of the 646 patients exposed to 30 mcg sufentanil or higher in the first hour of treatment, approximately 11% (72) of patients were ≥ 75 years of age and approximately 20% (126) patients were 65 to 75 years of age. The overall rate of adverse events and most common adverse events, such as nausea, tended to increase with age in patients who received sublingual sufentanil, although vomiting was less common in patients aged ≥ 75 years than in younger patients.

Respiratory depression is the chief risk for elderly patients treated with opioids, and has occurred after large initial doses were administered to patients who were not opioid-tolerant or when opioids were co-administered with other agents that depress respiration. As the dose of DSUVIA cannot be titrated, monitor geriatric patients closely for signs of central nervous system and respiratory depression or consider an alternate medication that can be titrated [see Warnings and Precautions (5.4)].

8.6 Hepatic Impairment

Because sufentanil is extensively metabolized in the liver, its clearance may decrease in patients with hepatic impairment. Monitor closely for adverse events such as respiratory depression, sedation, and hypotension [see Clinical Pharmacology (12.3)].

8.7 Renal Impairment

Sufentanil and its metabolites are known to be excreted by the kidney. No significant changes have been observed in subjects with mild or moderate renal impairment. Monitor closely for adverse events such as respiratory depression, sedation, and hypotension in patients with severe renal impairment [see Clinical Pharmacology (12.3)].

9 DRUG ABUSE AND DEPENDENCE

9.1 Controlled Substance

DSUVIA contains sufentanil citrate, a Schedule II controlled opioid agonist that can be abused and may produce drug dependence.

9.2 Abuse

DSUVIA contains sufentanil, a substance with a high potential for misuse and abuse, which can lead to the development of substance use disorder, including addiction [see Warnings and Precautions (5.3)].

Misuse is the intentional use, for therapeutic purposes, of a drug by an individual in a way other than prescribed by a healthcare provider or for whom it was not prescribed.

Abuse is the intentional, non-therapeutic use of a drug, even once, for its desirable psychological or physiological effects.

Drug addiction is a cluster of behavioral, cognitive, and physiological phenomena that may include a strong desire to take the drug, difficulties in controlling drug use (e.g., continuing drug use despite harmful consequences, giving a higher priority to drug use than other activities and obligations), and possible tolerance or physical dependence.

Misuse and abuse of DSUVIA increases risk of overdose, which may lead to central nervous system and respiratory depression, hypotension, seizures, and death. The risk is increased with concurrent abuse of DSUVIA with alcohol and/or other CNS depressants. Abuse of and addiction to opioids in some individuals may not be accompanied by concurrent tolerance and symptoms of physical dependence. In addition, abuse of opioids can occur in the absence of addiction.

All patients treated with opioids require careful and frequent reevaluation for signs of misuse, abuse, and addiction, because use of opioid analgesic products carries the risk of addiction even under appropriate medical use. Patients at high risk of DSUVIA abuse include those with a history of prolonged use of any opioid, including products containing sufentanil, those with a history of drug or alcohol abuse, or those who use DSUVIA in combination with other abused drugs.

“Drug-seeking” behavior is very common in persons with substance use disorders. Drug-seeking tactics include emergency calls or visits near the end of office hours, refusal to undergo appropriate examination, testing, or referral, repeated “loss” of prescriptions, tampering with prescriptions and reluctance to provide prior medical records or contact information for other treating health care provider(s). “Doctor shopping” (visiting multiple prescribers to obtain additional prescriptions) is common among people who abuse drugs and people with substance use disorder. Preoccupation with achieving adequate pain relief can be appropriate behavior in a patient with inadequate pain control.

DSUVIA, like other opioids, can be diverted for nonmedical use into illicit channels of distribution. Careful record-keeping of prescribing information, including quantity, frequency, and renewal requests, as required by state and federal law, is strongly advised.

Proper assessment of the patient, proper prescribing practices, periodic reevaluation of therapy, and proper dispensing and storage are appropriate measures that help to limit abuse of opioid drugs.

9.3 Dependence

Both tolerance and physical dependence can develop during use of opioid therapy.

Tolerance is a physiological state characterized by a reduced response to a drug after repeated administration (i.e., a higher dose of a drug is required to produce the same effect that was once obtained at a lower dose).

Physical dependence is a state that develops as a result of a physiological adaptation in response to repeated drug use, manifested by withdrawal signs and symptoms after abrupt discontinuation or a significant dose reduction of a drug.

Withdrawal may be precipitated through the administration of drugs with opioid antagonist activity (e.g., naloxone, nalmefene), mixed agonist/antagonist analgesics (e.g., pentazocine, butorphanol, nalbuphine), or partial agonists (e.g., buprenorphine). Physical dependence may not occur to a clinically significant degree until after several days to weeks of continued use.

Infants born to mothers physically dependent on opioids will also be physically dependent and may exhibit respiratory difficulties and withdrawal signs [see Use in Specific Populations (8.1)].

10 OVERDOSAGE

Clinical Presentation

Acute overdose with sufentanil can be manifested by respiratory depression, somnolence progressing to stupor or coma, skeletal muscle flaccidity, cold and clammy skin, constricted pupils, and, in some cases, pulmonary edema, bradycardia, hypotension, hypoglycemia, partial or complete airway obstruction, atypical snoring, and death. Marked mydriasis rather than miosis may be seen with hypoxia in overdose situations [see Clinical Pharmacology (12.2)]. Toxic leukoencephalopathy has been reported after opioid overdose and can present hours, days, or weeks after apparent recovery from the initial intoxication.

Treatment of Overdose

In case of overdose, priorities are the reestablishment of a patent and protected airway and institution of assisted or controlled ventilation, if needed. Employ other supportive measures (including oxygen and vasopressors) in the management of circulatory shock and pulmonary edema as indicated. Cardiac arrest or arrhythmias will require advanced life-support measures.

For clinically significant respiratory or circulatory depression secondary to sufentanil overdose, administer an opioid overdose reversal agent, such as naloxone or nalmefene.

Because the duration of opioid reversal is expected to be less than the duration of action of sufentanil in DSUVIA, carefully monitor the patient until spontaneous respiration is reliably re-established. If the response to an opioid overdose reversal agent is suboptimal or only brief in nature, administer additional antagonist as directed by the product’s prescribing information.

11 DESCRIPTION

DSUVIA contains one 30 mcg sufentanil tablet housed in a disposable single-dose applicator (SDA). The DSUVIA tablet is an immediate release formulation intended for sublingual administration. Each tablet is blue, flat-faced with a diameter of 3 mm.
The IUPAC chemical name for sufentanil is N-[4-(methoxymethyl)-1-[2-(2-thienyl)ethyl]-4-piperidinyl]-N-phenylpropanamide citrate. Sufentanil citrate has a molecular weight of 578.4 (molecular weight of free sufentanil base is 386.55), its empirical formula is C 28H 38N 2O 9S ● C 6H 8N 2O 7, and its chemical structure is shown below:

DSUVIA tablets inactive ingredients are: mannitol; dicalcium phosphate anhydrous; hypromellose; croscarmellose sodium; FD&C Blue #2; stearic acid and magnesium stearate.

12 CLINICAL PHARMACOLOGY

12.1 Mechanism of Action

Sufentanil is an opioid agonist and is relatively selective for the mu-opioid receptor, although it can bind to other opioid receptors at higher doses.
The principle therapeutic action of sufentanil is analgesia and sedation, thought to be mediated through opioid-specific receptors throughout the CNS. Like all full opioid agonists, there is no ceiling effect to analgesia.

12.2 Pharmacodynamics

Effects on the Central Nervous System
Sufentanil produces respiratory depression by direct action on brain stem respiratory centers. The respiratory depression involves both a reduction in the responsiveness of the brain stem respiratory centers to increases in carbon dioxide tension and to electrical stimulation.
Sufentanil causes miosis, even in total darkness. Pinpoint pupils are a sign of opioid overdose but are not pathognomonic (e.g., pontine lesions of hemorrhagic or ischemic origins may produce similar findings). Marked mydriasis rather than miosis may be seen due to hypoxia in overdose situations.
Effects on the Gastrointestinal Tract and Other Smooth Muscle
Sufentanil causes a reduction in motility associated with an increase in smooth muscle tone in the antrum of the stomach and duodenum. Digestion of food in the small intestine is delayed and propulsive contractions are decreased. Propulsive peristaltic waves in the colon are decreased, while tone may be increased to the point of spasm resulting in constipation. Other opioid-induced effects may include a reduction in biliary and pancreatic secretions, spasm of sphincter of Oddi, transient elevations in serum amylase, and opioid-induced esophageal dysfunction (OIED).
Effects on the Cardiovascular System
Sufentanil produces peripheral vasodilation which may result in orthostatic hypotension or syncope. Manifestations of histamine release and/or peripheral vasodilation may include pruritus, flushing, red eyes and sweating and/or orthostatic hypotension.
Effects on the Endocrine System
Opioids inhibit the secretion of adrenocorticotropic hormone (ACTH), cortisol, and luteinizing hormone (LH) in humans. They also stimulate prolactin, growth hormone (GH) secretion, and pancreatic secretion of insulin and glucagon [see Adverse Reactions (6.2)].
Use of opioids for an extended period of time may influence the hypothalamic-pituitary-gonadal axis, leading to androgen deficiency that may manifest as low libido, impotence, erectile dysfunction, amenorrhea, or infertility. The causal role of opioids in the clinical syndrome of hypogonadism is unknown because the various medical, physical, lifestyle, and psychological stressors that may influence gonadal hormone levels have not been adequately controlled for in studies conducted to date [see Adverse Reactions (6.2)].
Effects on the Immune System
Opioids have been shown to have a variety of effects on components of the immune system in in vitro and animal models. The clinical significance of these findings is unknown. Overall, the effects of opioids appear to be modestly immunosuppressive.

Effects on the Respiratory System
All opioid mu-receptor agonists, including DSUVIA, produce dose-dependent respiratory depression. The risk of respiratory depression is less in patients receiving chronic opioid therapy who develop tolerance to respiratory depression and other opioid effects.
Serious or fatal respiratory depression can occur even at recommended doses. Although not observed with DSUVIA in the clinical trial, sufentanil given rapidly by intravenous injection in large doses may interfere with respiration by causing rigidity in the muscles of respiration [see Warnings and Precautions (5.4)].

12.3 Pharmacokinetics

Absorption
A single sublingual administration of DSUVIA has a bioavailability of approximately 53% relative to a one-minute IV sufentanil infusion of 30 mcg. Compared to IV administration, sublingual Cmax values were 17-fold lower. The sublingual route of administration of sufentanil avoids intestinal and hepatic first-pass effects, both which severely limit bioavailability of swallowed (oral) sufentanil sublingual tablet (9%). Following a single dose of DSUVIA, the mean AUC0-inf is 278 h*pg/mL, the average Cmax of 63.1 pg/mL occurs at a median Tmax of 1.00 hour. After 12 multiple hourly doses over 11 hours, the geometric mean for the AUC within a dosing interval (AUC0-60min) and Cmax values were increased by 3.7-fold and 2.3-fold greater compared to single-dose administration, respectively. Steady-state plasma concentrations were achieved after 7 doses (Figure 1).
Figure 1: Sufentanil Concentration-Time Values: Single vs. Consecutive Repeat Doses (12 DSUVIA Doses)

Distribution
Plasma protein binding of sufentanil, related to the alpha acid glycoprotein concentration, was approximately 93% in healthy males, 91% in mothers and 79% in neonates.

Elimination
Following a single dose of DSUVIA, the mean terminal half-life is 13.4 hours, and the mean apparent plasma clearance is 108 L/hour.
Metabolism: The liver and small intestine are the major sites of biotransformation
Excretion: Approximately 80% of the IV administered dose of sufentanil is excreted within 24 hours and only 2% of the dose is eliminated as unchanged drug.
Specific Populations
Clearance is not significantly affected by race, sex, mild or moderate renal impairment based on the population pharmacokinetics.
Drug Interaction Study
Co-administration of a single dose of sufentanil sublingual tablet 15 mcg with a strong CYP3A4 inhibitor, ketoconazole, resulted in 77% and 19% greater AUC0-inf and Cmax values of sufentanil, respectively, compared to its administration alone.

13 NONCLINICAL TOXICOLOGY

13.1 Carcinogenesis, Mutagenesis, Impairment of Fertility

Carcinogenesis
Long-term studies in animals to evaluate the carcinogenic potential of sufentanil have not been conducted.
Mutagenesis:
Sufentanil was not genotoxic in the in vitro bacterial reverse mutation assay (Ames assay) or in the in vivo rat bone marrow micro-nucleus assay.
Impairment of Fertility
Fertility and early embryonic development studies were conducted in male and female rats treated with 0.005, 0.02 or 0.08 mg/kg sufentanil IV for 56 days and 14 days prior to mating through gestation respectively. Increased mortality was noted in all treatment groups.
Lower pregnancy rates were noted following treatment of males at doses of 0.02 and 0.08 mg/kg (0.6 and 2.2 times the maximum human daily dose of 360 mcg/60 kg, based on a body surface area comparison), suggesting the potential for an adverse effect on fertility in males. Increased resorption of fetuses and reduced litter size was noted in the high dose females (2.2 times the maximum human daily dose of 360 mcg/60 kg, based on a body surface area comparison) suggesting the potential for fetotoxicity, likely due to maternal toxicity.

14 CLINICAL STUDIES

The efficacy and safety of DSUVIA were evaluated in one randomized, double-blind, placebo-controlled trial which enrolled 161 patients (age 18 to 69 years) with acute postoperative pain (pain intensity of ≥ 4 on a 0-10 Numeric Rating Scale [NRS]) after abdominal surgery (studied up to 48 hours) (Study SAP301, NCT# 02356588). Patients were dosed with DSUVIA 30 mcg or placebo as needed with a minimum of 60 minutes between doses. Morphine sulfate 1 mg IV was available as rescue medication.
The primary efficacy endpoint was the time-weighted summed pain intensity difference over 12 hours (SPID12). Patients using DSUVIA had a statistically significantly higher SPID12 than patients using placebo. Least squares means of pain intensity difference from baseline over 24 hours for the abdominal surgery study are shown in Figure 2. Median time to onset of meaningful pain relief (measured using the double stopwatch method) was 54 minutes for the DSUVIA group and 84 minutes for the placebo group. Approximately 22% of patients in the DSUVIA group and 65% of patients in the placebo group took rescue medication within the first 12 hours of the treatment phase.
Figure 2: Least Squares Mean of Pain Intensity Difference by Evaluation Time Point over the 24-Hour Study Period: Abdominal Surgery ITT Population

PID = pain intensity difference; ITT = intent-to-treat; LS = least squares; SEM = standard error of the mean

16 HOW SUPPLIED/STORAGE AND HANDLING

16.1 How Supplied

Each DSUVIA tablet 30 mcg is housed in a single-dose applicator (SDA) and packaged within a tamper-evident laminate foil pouch. For distribution there is one presentation:
• NDC 61621-430-11 (10 pouches per carton)
The SDA should be disposed in biohazard waste after administration of DSUVIA.
Instruct the healthcare provider to take steps to store DSUVIA securely and to dispose of any dropped or misplaced DSUVIA tablets according to institutional CII procedures.

16.2 Storage and Handling

Store DSUVIA at room temperature 20-25 ºC, excursions allowed 15-30 ºC in a secure, limited access location, in accordance with institutional procedures for CII products.

17 PATIENT COUNSELING INFORMATION

Increased Risk of Overdose and Death in Children Due to Accidental Exposure

Inform patients that accidental exposure, especially by children, may result in respiratory depression or death [see Warnings and Precautions (5.1)].

Addiction, Abuse, and Misuse

Inform patients that the use of DSUVIA, even when taken as recommended, can result in addiction, abuse, and misuse, which can lead to overdose and death [see Warnings and Precautions (5.4)]. Instruct patients not to share DSUVIA with others and to take steps to protect DSUVIA from theft or misuse.

Life-Threatening Respiratory Depression

Inform patients of the risk of life-threatening respiratory depression, including information that the risk is greatest when starting DSUVIA [see Warnings and Precautions (5.4)].

Hyperalgesia and Allodynia

Advise patients to inform their healthcare provider if they experience symptoms of hyperalgesia, including worsening pain, increased sensitivity to pain, or new pain [see Warnings and Precautions (5.7), and Adverse Reactions (6.2)].

Serotonin Syndrome

Inform patients that opioids could cause a rare but potentially life-threatening condition called serotonin syndrome resulting from concomitant administration of serotonergic drugs. Warn patients of the symptoms of serotonin syndrome and to seek medical attention right away if symptoms develop after discharge from the hospital. Instruct patients to inform their physicians if they are taking, or plan to take serotonergic medications. [see Warnings and Precautions (5.8), and Drug Interactions (7)].

Important Administration Instructions

Advise patients to allow DSUVIA to dissolve under the tongue and not to chew or swallow the tablet. Advise patients not to eat or drink and to minimize talking for 10 minutes after each dose of DSUVIA.

Adrenal Insufficiency

Inform patients that opioids could cause adrenal insufficiency, a potentially life-threatening condition. Adrenal insufficiency may present with non-specific symptoms and signs such as nausea, vomiting, anorexia, fatigue, weakness, dizziness, and low blood pressure. Advise patients to seek medical attention if they experience a constellation of these symptoms [see Warnings and Precautions (5.10)].

Hypotension

Inform patients that DSUVIA may cause orthostatic hypotension and syncope. Instruct patients how to recognize symptoms of low blood pressure and how to reduce the risk of serious consequences should hypotension occur (e.g., sit or lie down, carefully rise from a sitting or lying position) [see Contraindications (4), and Warnings and Precautions (5.11)].

Anaphylaxis

Inform patients that anaphylaxis has been reported with ingredients contained in DSUVIA. Advise patients how to recognize such a reaction and when to seek medical attention [see Contraindications (4), and Adverse Reactions (6)].

Pregnancy

Embryo-Fetal Toxicity

Inform female patients of reproductive potential that DSUVIA can (or may) cause fetal harm and to inform the prescriber of a known or suspected pregnancy [see Use in Specific Populations (8.3)].

Lactation

Advise nursing mothers to carefully observe infants for increased sleepiness (more than usual), breathing difficulties, or limpness. Instruct nursing mothers to seek immediate medical care if they notice these signs [see Use in Specific Populations (8.2)].

Marketed By: AcelRx Pharmaceuticals, Inc., Hayward, CA

PL-6410 Rev F

PACKAGE LABEL.PRINCIPAL DISPLAY PANEL

SUFENTANIL CARTON

SUFENTANIL CONTAINER POUCH BACK FOLDOUT

SUFENTANIL CONTAINER POUCH BACK BASE PANEL
SUFENTANIL CONTAINER POUCH FRONT